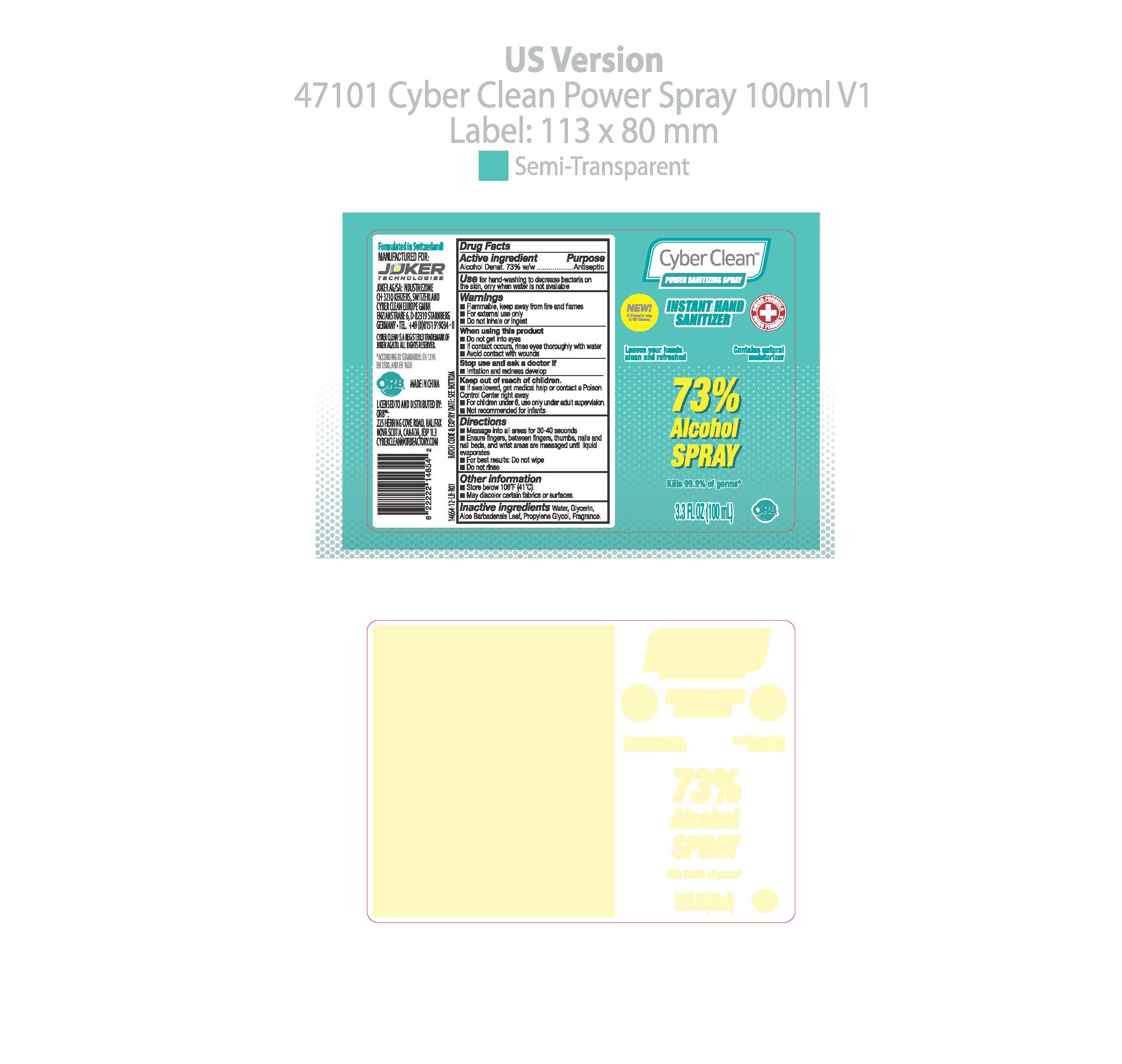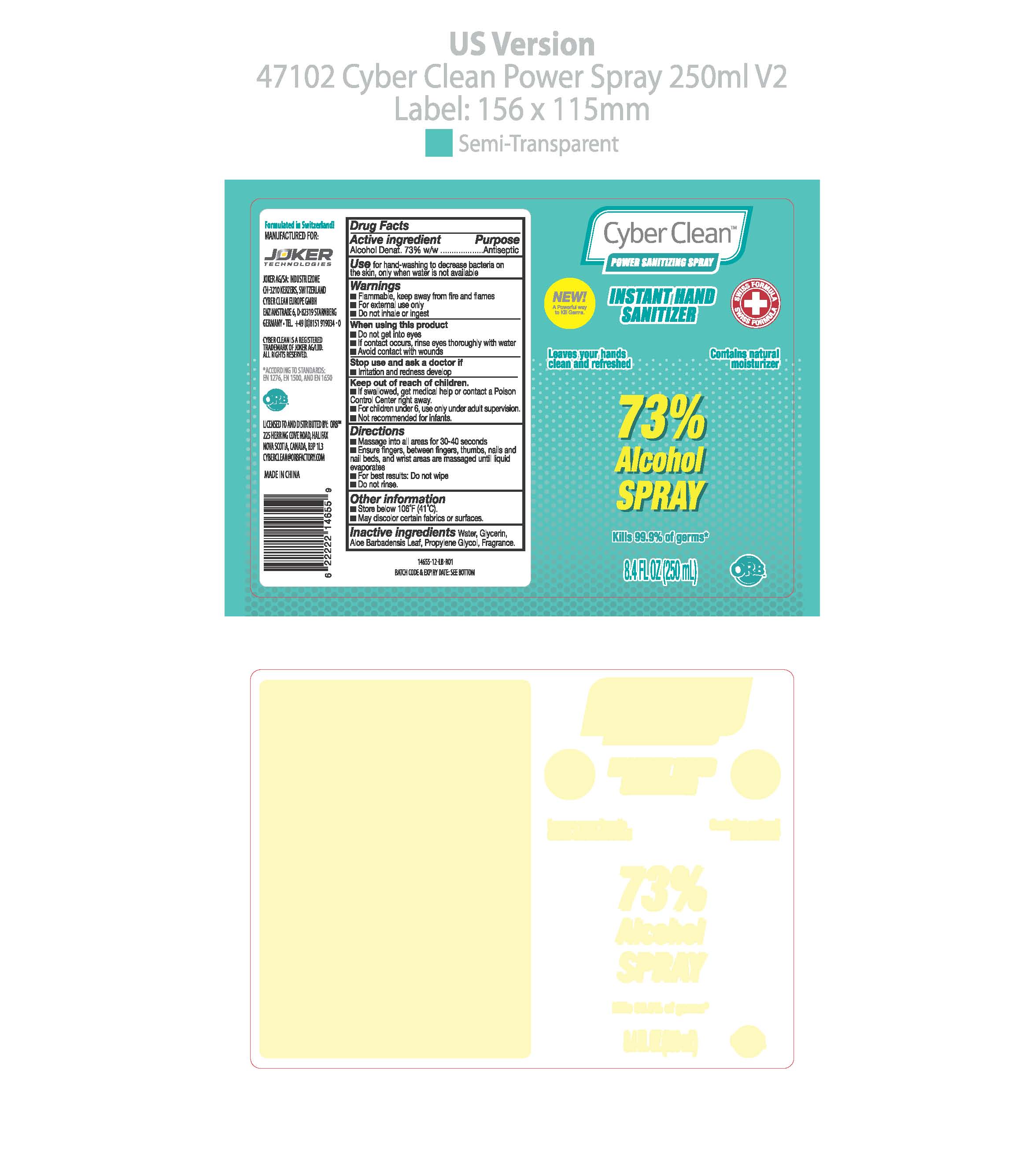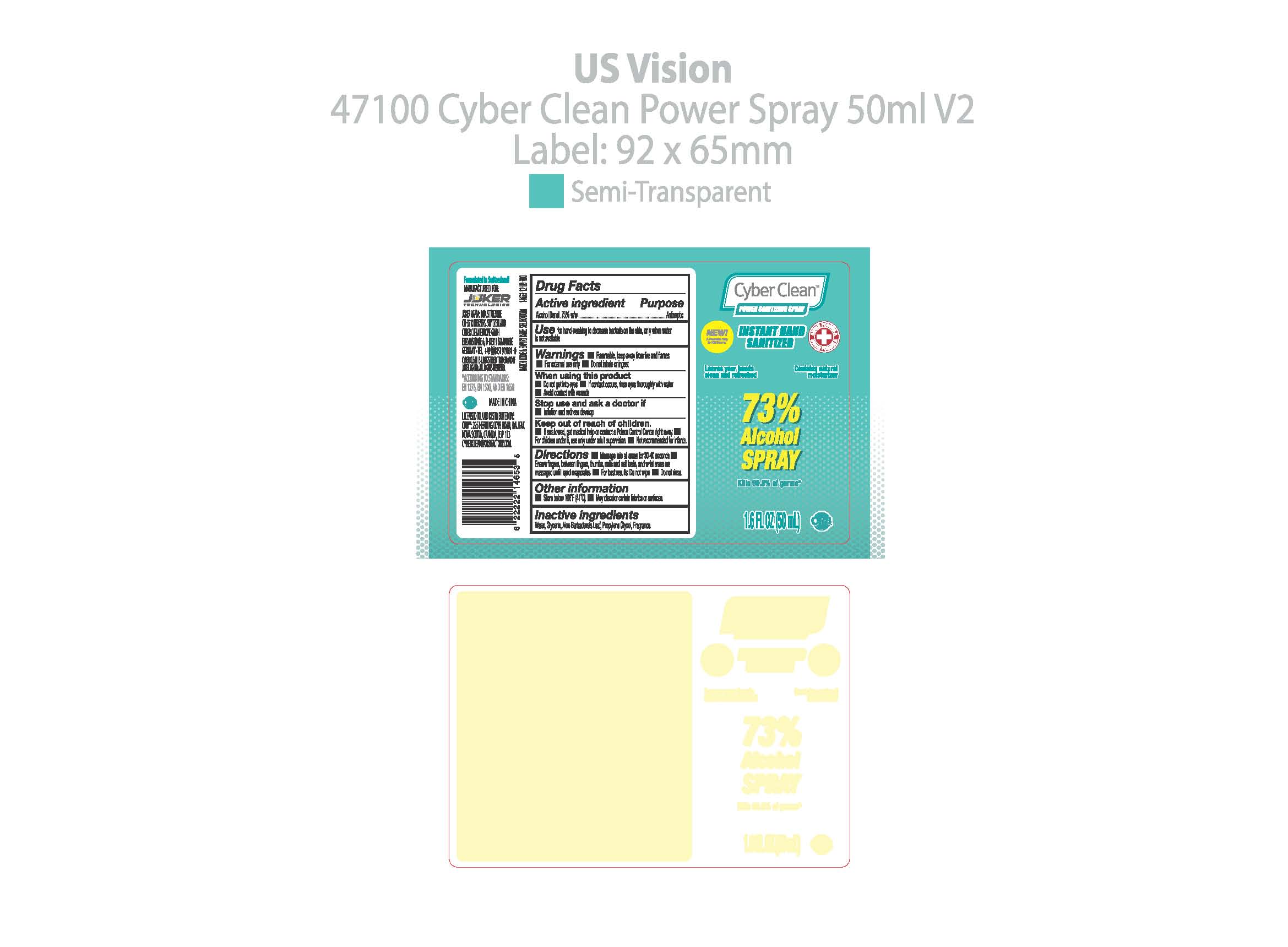 DRUG LABEL: Cyber Clean Power SanitizingSpray
NDC: 75757-901 | Form: LIQUID
Manufacturer: JOKER AG
Category: otc | Type: HUMAN OTC DRUG LABEL
Date: 20210126

ACTIVE INGREDIENTS: ALCOHOL 73 g/100 g
INACTIVE INGREDIENTS: PROPYLENE GLYCOL; TERT-BUTYL ALCOHOL; GLYCERIN; WATER; ALOE VERA LEAF; PELARGONIUM GRAVEOLENS FLOWER OIL; DENATONIUM BENZOATE

Cyber Clean Power SanitizingSpray

Cyber Clean Power SanitizingSpray

Active Ingredient(s)

Alcohol 73% w/w. Purpose: Antiseptic

Purpose

Antiseptic, Cyber Clean Power SanitizingSpray

Use

Cyber Clean Power SanitizingSpray to help reduce bacteria that potentially can cause disease. For use when soap and water are not available.

Warnings

For external use only. Flammable. Keep away from heat or flame

Do not use

- in children less than 2 months of age
- on open skin wounds

When using this product keep out of eyes, ears, and mouth. In case of contact with eyes, rinse eyes thoroughly with water.
Stop use and ask a doctor if irritation or rash occurs. These may be signs of a serious condition.
Keep out of reach of children. If swallowed, get medical help or contact a Poison Control Center right away.

Stop use and ask a doctor if irritation or rash occurs. These may be signs of a serious condition.

Keep out of reach of children. If swallowed, get medical help or contact a Poison Control Center right away.

Directions

- Massage into all areas for 30-40 seconds
- Ensure fingers, betwuun fingers, thumbs, nails and nail beds, and wrist areas are massaged until liquid evaporates
- For best results: Do not wipe
- Do not rinse.
- Supervise children under 6 years of age when using this product to avoid swallowing.

Other information

- Store between 15-30C (59-86F)
- Avoid freezing and excessive heat above 40C (104F)

Inactive ingredients

Water
Glycerin
Aloe Vera Leaf
Propylene Glycol
Tert-butyl alcohol
Denatonium benzoate
Pelargonium Graveolens Flower Oil